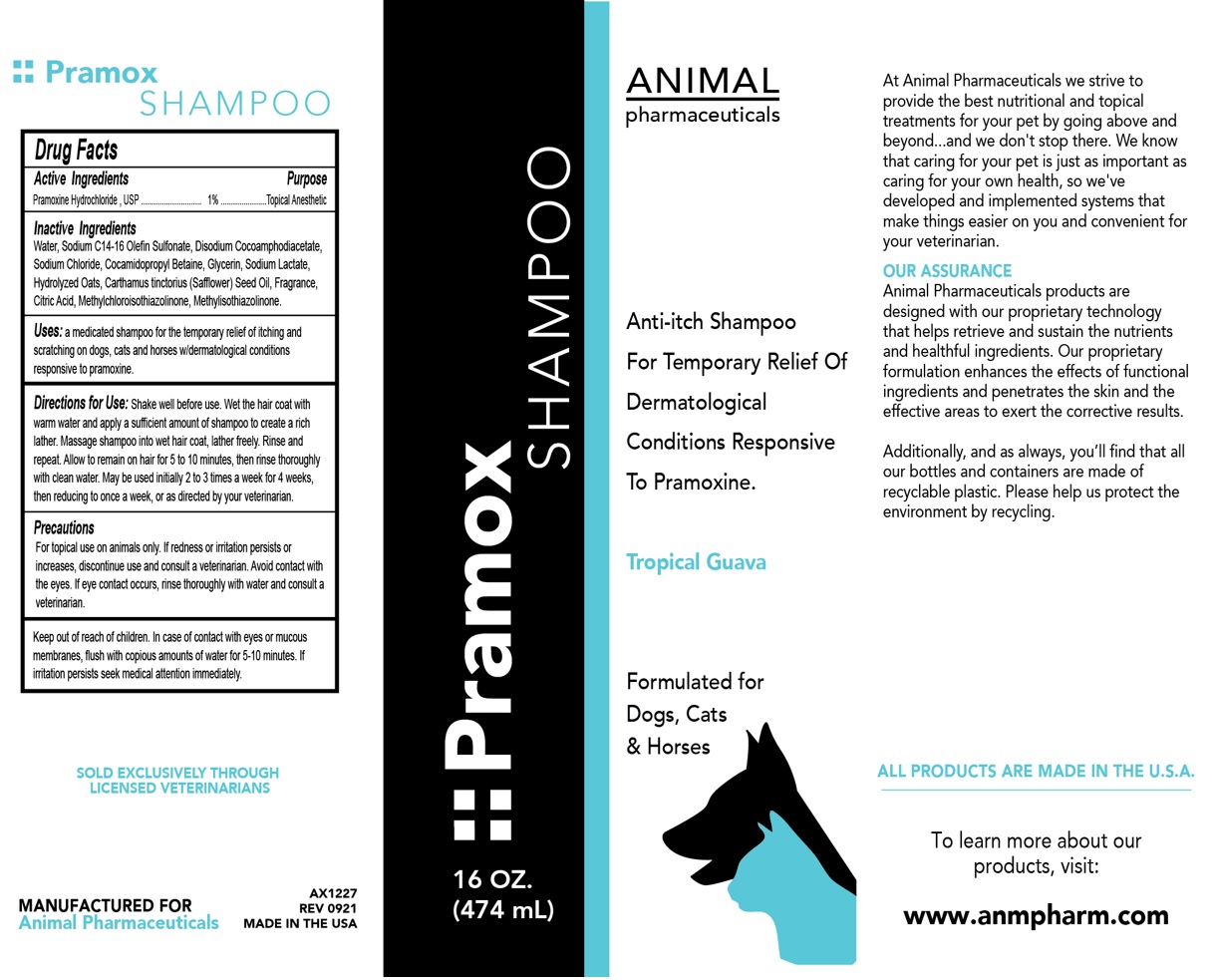 DRUG LABEL: Pramox
NDC: 68898-124 | Form: SHAMPOO
Manufacturer: Animal Pharmaceuticals
Category: animal | Type: OTC ANIMAL DRUG LABEL
Date: 20211018

ACTIVE INGREDIENTS: PRAMOXINE HYDROCHLORIDE 1 g/100 mL
INACTIVE INGREDIENTS: WATER; SODIUM C14-16 OLEFIN SULFONATE; DISODIUM COCOAMPHODIACETATE; SODIUM CHLORIDE; COCAMIDOPROPYL BETAINE; GLYCERIN; SODIUM LACTATE; OAT; SAFFLOWER OIL; CITRIC ACID MONOHYDRATE; METHYLCHLOROISOTHIAZOLINONE; METHYLISOTHIAZOLINONE

Pramox SHAMPOO

Active Ingredients

Pramoxine Hydrochloride , USP 1%

Purpose

Topical Anesthetic

Inactive Ingredients

Water, Sodium C14-16 Olefin Sulfonate, Disodium Cocoamphodiacetate, Sodium Chloride, Cocamidopropyl Betaine, Glycerin, Sodium Lactate, Hydrolyzed Oats, Carthamus tinctorius (Safflower) Seed Oil, Fragrance, Citric Acid, Methylchloroisothiazolinone, Methylisothiazolinone.

Uses:

a medicated shampoo for the temporary relief of itching and scratching on dogs, cats and horses with dermatological conditions responsive to pramoxine.

Directions for Use:

Shake well before use. Wet the hair coat with warm water and apply a sufficient amount of shampoo to create a rich lather. Massage shampoo into wet hair coat, lather freely. Rinse and repeat. Allow to remain on hair for 5 to 10 minutes, then rinse thoroughly with clean water. May be used initially 2 to 3 times a week for 4 weeks, then reducing to once a week, or as directed by your veterinarian.

Precautions

For topical use on animals only. If redness or irritation persists or increases, discontinue use and consult a veterinarian. Avoid contact with the eyes. If eye contact occurs, rinse thoroughly with water and consult a veterinarian.

Keep out of reach of children. In case of contact with eyes or mucous membranes, flush with copious amounts of water for 5-10 minutes. If irritation persists seek medical attention immediately.

Anti-itch Shampoo

For Temporary Relief of Dermatological Conditions Responsive To Pramoxine.

Tropical Guava

Formulated for Dogs, Cats & Horses

At Animal Pharmaceuticals we strive to provide the best nutritional and topical treatments for your pet by going above and beyond...and we don't stop there. We know that caring for your pet is just as important as caring for your own health, so we've developed and implemented systems that make things easier on you and convenient for your veterinarian.

OUR ASSURANCE
Animal Pharmaceuticals products are designed with our proprietary technology that helps retrieve and sustain the nutrients and healthful ingredients. Our proprietary formulation enhances the effects of functional ingredients and penetrates the skin and the effective areas to exert the corrective results.

Additionally, and as always, you'll find that all our bottles and containers are made of recyclable plastic. Please help us protect the environment by recycling.

ALL PRODUCTS ARE MADE IN THE U.S.A

To learn more about our products, visit:

www.anmpharm.com

SOLD EXCLUSIVELY THROUGH LICENSED VETERINARIANS

MANUFACTURED FOR
Animal Pharmaceuticals

MADE IN THE USA